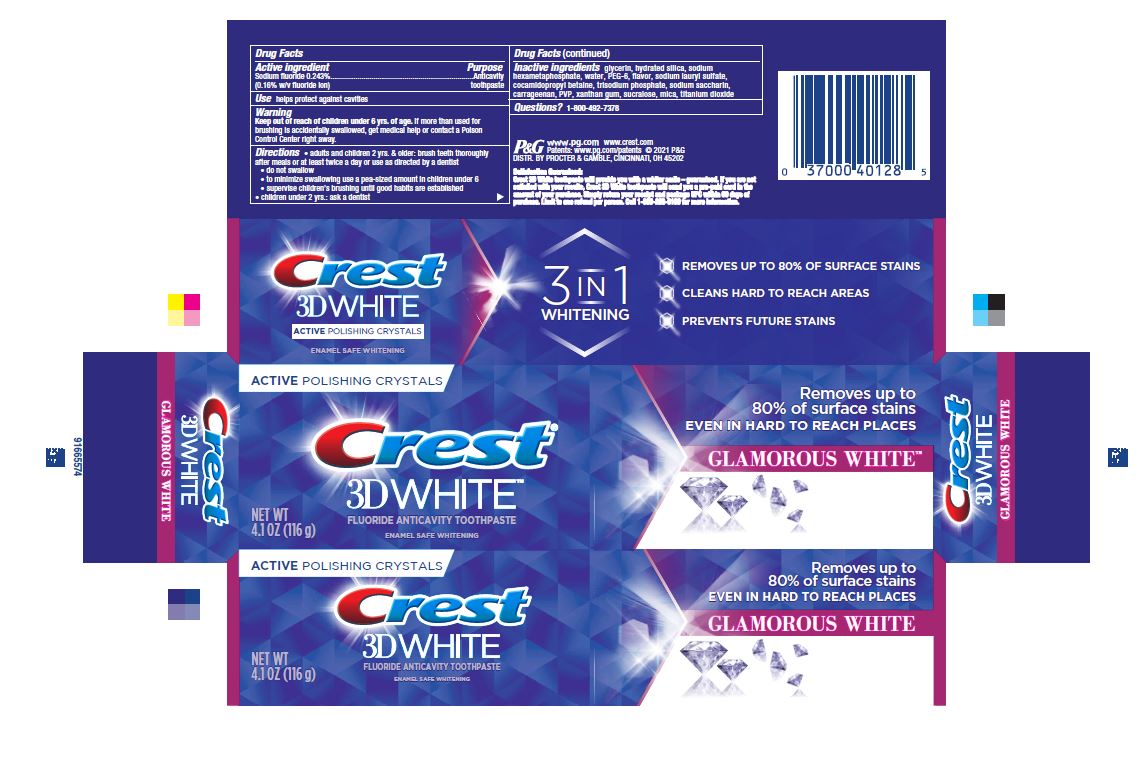 DRUG LABEL: Crest 3D White
NDC: 69423-914 | Form: PASTE, DENTIFRICE
Manufacturer: The Procter & Gamble Manufacturing Company
Category: otc | Type: HUMAN OTC DRUG LABEL
Date: 20251217

ACTIVE INGREDIENTS: SODIUM FLUORIDE 1.6 mg/1 g
INACTIVE INGREDIENTS: HYDRATED SILICA; WATER; COCAMIDOPROPYL BETAINE; SACCHARIN SODIUM; XANTHAN GUM; SUCRALOSE; MICA; TITANIUM DIOXIDE; POLYETHYLENE GLYCOL 300; GLYCERIN; SODIUM POLYMETAPHOSPHATE; SODIUM PHOSPHATE, TRIBASIC, ANHYDROUS; SODIUM LAURYL SULFATE; CARRAGEENAN; POVIDONE, UNSPECIFIED

Crest 3D White Glamorous White

Drug Facts

Active ingredient

Sodium fluoride 0.243% (0.16% w/v fluoride ion)

Purpose

Anticavity toothpaste

Use

helps protect against cavities

Warning

Keep out of reach of children under 6 yrs. of age. If more than used for brushing is accidentally swallowed, get medical help or contact a Poison Control Center right away.

Directions

- adults and children 2 yrs. & older: brush teeth thoroughly after meals or at least twice a day or use as directed by a dentist
- do not swallow
- to minimize swallowing use a pea-sized amount in children under 6
- supervise children's brushing until good habits are established
- children under 2 yrs.: ask a dentist

Inactive ingredients

glycerin, hydrated silica, sodium hexametaphosphate, water, PEG-6, flavor, sodium lauryl sulfate, cocamidopropyl betaine, trisodium phosphate, sodium saccharin, carrageenan, PVP, xanthan gum, sucralose, mica, titanium dioxide

Questions?

1-800-492-7378

DISTR. BY PROCTER & GAMBLE, CINCINNATI, OH 45202

PRINCIPAL DISPLAY PANEL - 116 g Tube Carton

ACTIVE POLISHING CRYSTALS

Crest®
3D WHITE™
FLUORIDE ANTICAVITY TOOTHPASTE

NET WT 4.1 OZ (116 g)

ENAMEL SAFE WHITENING
Removes up to

80% of surface stains
EVEN IN HARD TO REACH PLACES
GLAMOROUS WHITE™